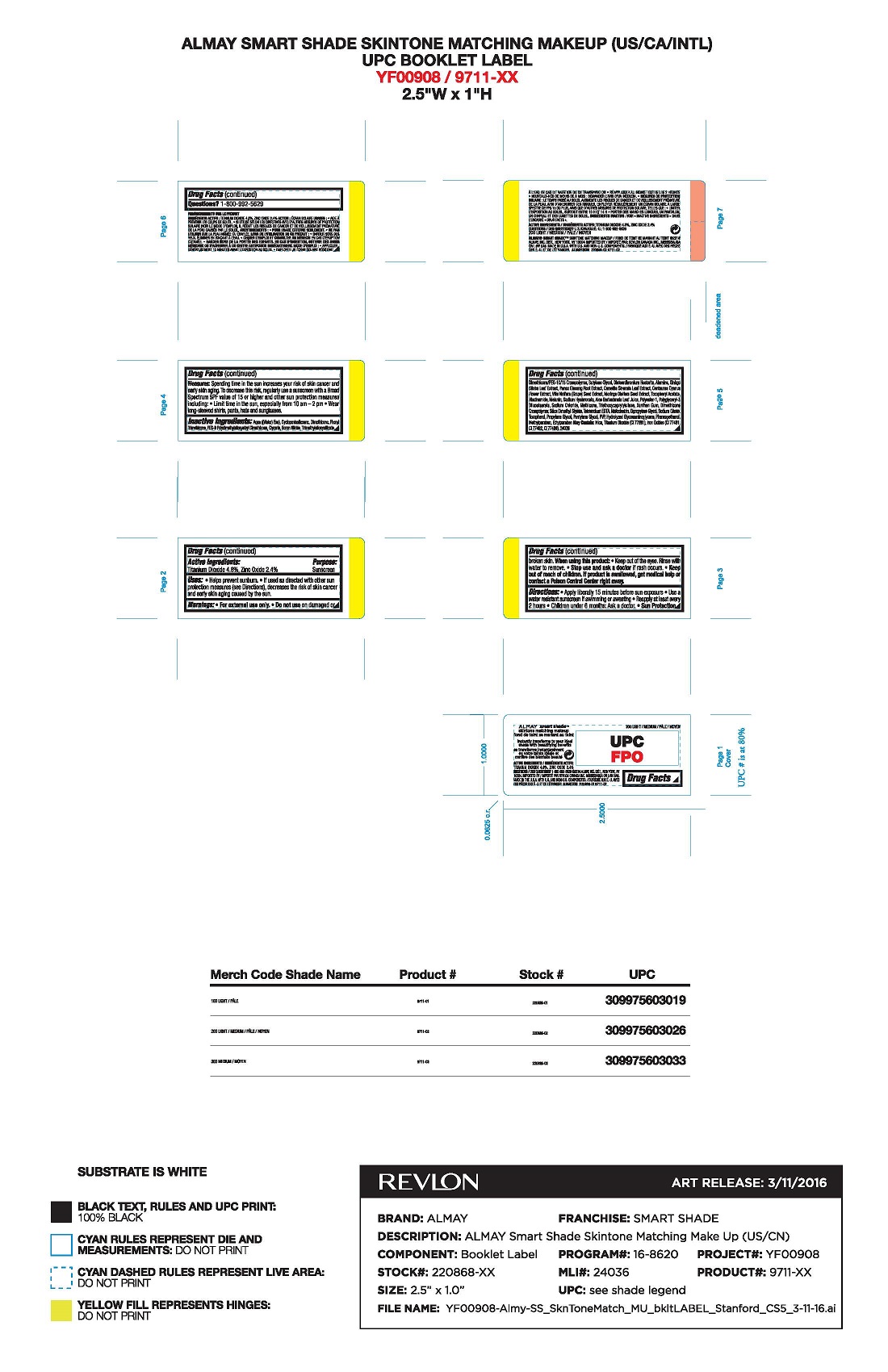 DRUG LABEL: Almay Smart Shade Skintone Matching Makeup
NDC: 0311-0784 | Form: LIQUID
Manufacturer: Almay, Inc.
Category: otc | Type: HUMAN OTC DRUG LABEL
Date: 20241231

ACTIVE INGREDIENTS: TITANIUM DIOXIDE 4.8 mg/1 mL; ZINC OXIDE 2.4 mg/1 mL
INACTIVE INGREDIENTS: WATER; CYCLOPENTASILOXANE; PHENYL TRIMETHICONE; PEG-9 POLYDIMETHYLSILOXYETHYL DIMETHICONE; GLYCERIN; TRIMETHYLSILOXYSILICATE (M/Q 1.0-1.2); BUTYLENE GLYCOL; DISTEARDIMONIUM HECTORITE; ALUMINUM OXIDE; NIACINAMIDE; HYALURONATE SODIUM; ALOE VERA LEAF; POLYGLYCERYL-3 DIISOSTEARATE; SODIUM CHLORIDE; METHICONE (20 CST); TRIETHOXYCAPRYLYLSILANE; XANTHAN GUM; SILICA DIMETHYL SILYLATE; MALTODEXTRIN; DIPROPYLENE GLYCOL; SODIUM CITRATE; DIMETHICONE; TOCOPHEROL; PROPYLENE GLYCOL; PENTYLENE GLYCOL; PHENOXYETHANOL; HYDROLYZED GLYCOSAMINOGLYCANS (BOVINE; 50000 MW); METHYLPARABEN; FERROSOFERRIC OXIDE; ETHYLHEXYLGLYCERIN; GINKGO; ETHYLPARABEN; BORON NITRIDE; .ALPHA.-TOCOPHEROL ACETATE; ASIAN GINSENG; GREEN TEA LEAF; CENTAUREA CYANUS FLOWER; VITIS VINIFERA SEED; MORINGA OLEIFERA LEAF; MELANIN SYNTHETIC (TYROSINE, PEROXIDE); EDETATE DISODIUM; MORINGA OLEIFERA SEED; MICA; FERRIC OXIDE YELLOW; HYDROGEN DIMETHICONE (13 CST); FERRIC OXIDE RED; SILICON DIOXIDE; SODIUM BENZOATE; TETRASODIUM EDTA; DISODIUM PHOSPHATE; DIMETHICONE/PEG-10/15 CROSSPOLYMER; DIMETHICONE CROSSPOLYMER; POTASSIUM SORBATE; CITRIC ACID; PVP

Almay Smart Shade Skintone Matching Makeup - MEDIUM

Active Ingredients:

Titanium Dioxide: 4.8%

Zinc Oxide 2.4%

Purpose

Sunscreen

Uses:

•Helps prevent sunburn
•If used as directed with other sun protection measures (see Directions), decreases the risk of skin cancer and early skin aging caused by the sun

Warnings:

•For external use only
•Do notuse on damaged or broken skin
•When using this product: Keep out of eyes. Rinse with water to remove.
•Stop use and ask a doctor if a rash occurs
•Keep out of reach of children. If product is swallowed, get medical help or contact a Poison Control center right away

Directions

•Apply liberally 15 minutes before sun exposure
•Use a water resistant sunscreen if swimming or sweating
•Reapply at least every 2 hours
•Children under 6 months: Ask a doctor.

Sun Protection Measures

Spending time in the sun increases your risk of skin cancer and early skin aging. To decrease this risk, regularly use a sunscreen with a Broad Spectrum SPF value of 15 or higher and other sun protection measures including:
•Limit time in the sun, especially from 10 am - 2 pm
•Wear long-sleeved shirts, pants, hats and sunglasses.

Inactive Ingredients

Aqua ((Water) Eau), Cyclopentasiloxane, Dimethicone, Phenyl Trimethicone, PEG-9 Polydimethylsiloxyethyl Dimethicone, Glycerin, Boron Nitride, Trimethylsiloxysilicate, Dimethicone/PEG-10/15 Crosspolymer, Butylene Glycol, Disteardimonium Hectorite, Alumina, Ginkgo Biloba Leaf Extract, Panax Ginseng Root Extract, Camellia Sinensis Leaf Extract, Centaurea Cyanus Flower Extract, Vitis Vinifera (Grape) Seed Extract, Moringa Oleifera Seed Extract, Tocopheryl Acetate, Niacinamide, Melanin, Sodium Hyaluronate, Aloe Barbadensis Leaf Juice, Polyester-1, Polyglyceryl-3 Diisostearate, Sodium Chloride, Methicone, Triethoxycaprylylsilane, Xanthan Gum, Dimethicone Crosspolymer, Silica Dimethyl Silylate, Tetrasodium EDTA, Maltodextrin, Dipropylene Glycol, Sodium Citrate, Tocopherol, Propylene Glycol, Pentylene Glycol, PVP, Hydrolyzed Glycosaminoglycans, Phenoxyethanol, Methylparaben, Ethylparaben

DOSAGE AND ADMINISTRATION

Apply liberally 15 minutes before sun exposure.

KEEP OUT OF REACH OF CHILDREN

Keep out of the reach of children. If product is swallowed, get medical help or contact a Poison Control Center right away.

Principal Display Panel

Almay

Skintone Matching Makeup